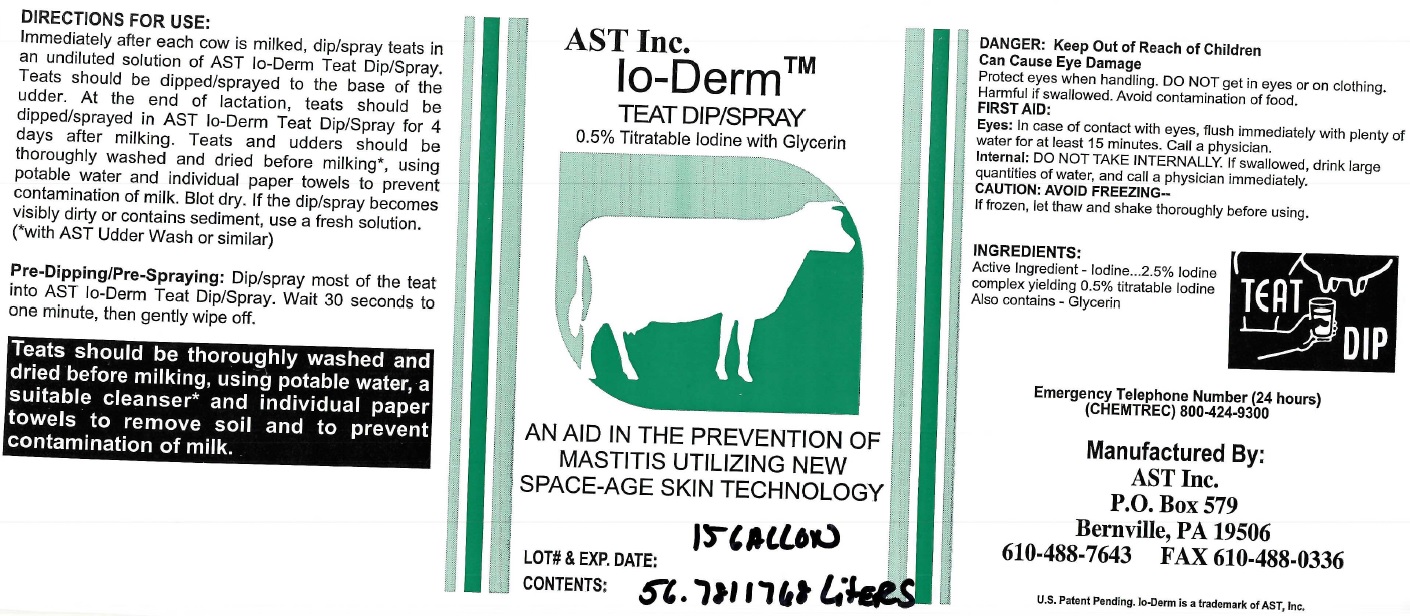 DRUG LABEL: AST Inc. Io-Derm TEAT DIP
NDC: 52657-0102 | Form: SOLUTION
Manufacturer: Advanced Skin Technologies Inc.
Category: animal | Type: OTC ANIMAL DRUG LABEL
Date: 20220218

ACTIVE INGREDIENTS: IODINE 25 mg/0.001 L
INACTIVE INGREDIENTS: GLYCERIN

AST Inc. Io-Derm TEAT DIP/SPRAY

DANGER:

Can Cause Eye Damage

Protect eyes when handling. DO NOT get in eyes or on clothing, Harmful if swallowed. Avoid contamination of food.

FIRST AID:

Eyes: In case of contact with eyes, flush immediately with plenty of water for at least 15 minutes. Call a physician.

Internal: DO NOT TAKE INTERNALLY. If swallowed, drink large quantities of water, and call a physician immediately.

CAUTION : AVOID FREEZING--

If frozen, let thaw and shake thoroughly before using.

INGREDIENTS:

Active Ingredient - Iodine 2.5% Iodine complex yielding 0.5% titratable Iodine Also contains - Glycerin

DIRECTIONS FOR USE:

Immediately after each cow is milked, dip/spray teats in an undiluted solution of AST lo-Derm Teat Dip/Spray. Teats should be dipped/sprayed to the base of the udder. At the end of lactation, teats should be dipped/sprayed in AST Lo-Derm Teat Dip.Spray for 4 days after milking. Teats and udders should be thoroughly washed and dried before milking*, using potable water and individual paper towels to prevent contamination of milk. Blot dry. If the dip/spray becomes visibley dirty or contains sediment, use a fresh solution.

(*with AST Udder Wash or similar)

Pre-Dipping/Pre-Spraying:

Dip/spray most of the teat into AST lo-Derm Teat Dip/Spray. Wait 30 seconds to one minute, then gently wipe off.

Teats should be thoroughly washed and dried before milking, using potable water, a suitable cleanser* and individual paper towels to remove soil and to prevent contamination of milk.